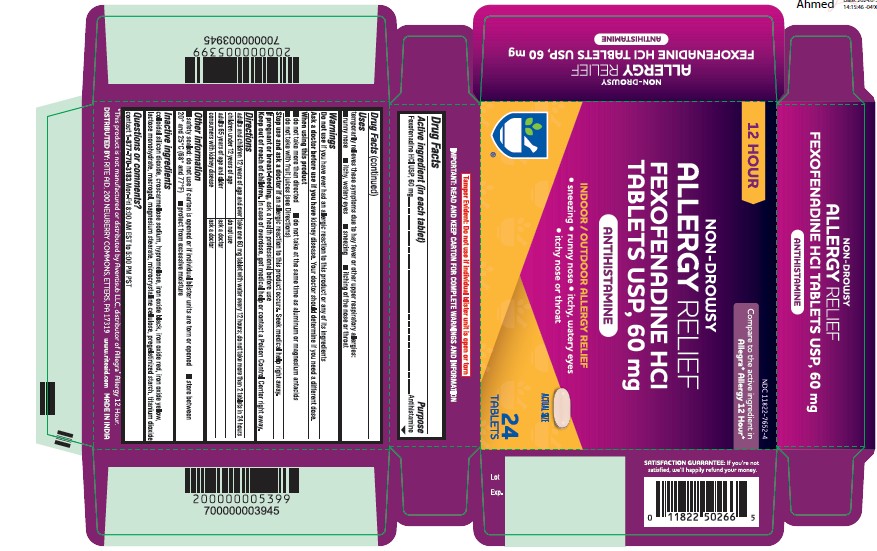 DRUG LABEL: Fexofenadine HCl
NDC: 11822-7652 | Form: TABLET
Manufacturer: Rite Aid
Category: otc | Type: HUMAN OTC DRUG LABEL
Date: 20251219

ACTIVE INGREDIENTS: FEXOFENADINE HYDROCHLORIDE 60 mg/1 1
INACTIVE INGREDIENTS: POLYETHYLENE GLYCOL 6000; SILICON DIOXIDE; LACTOSE MONOHYDRATE; MAGNESIUM STEARATE; FERRIC OXIDE RED; HYPROMELLOSE 2910 (15 MPA.S); STARCH, CORN; FERROSOFERRIC OXIDE; FERRIC OXIDE YELLOW; MICROCRYSTALLINE CELLULOSE; CROSCARMELLOSE SODIUM; TITANIUM DIOXIDE

Non-drowsy
Fexofenadine HCl Tablets USP, 60mg
Antihistamine
Indoor/Outdoor Allergy relief
• sneezing
• runny nose
• itchy, watery eyes
• itchy nose or throat

Active ingredient (in each tablet)

Fexofenadine HCl USP, 60 mg

Purpose

Antihistamine

Uses

temporarily relieves these symptoms due to hay fever or other upper respiratory allergies:
■ runny nose ■ itchy, watery eyes ■ sneezing ■ itching of the nose or throat

Warnings

Do not use if you have ever had an allergic reaction to this product or any of its ingredients

Ask a doctor before use if you have

kidney disease. Your doctor should determine if you need a different dose.

When using this product

■ do not take more than directed ■ do not take at the same time as aluminum or magnesium antacids
■ do not take with fruit juices (see Directions)

Stop use and ask a doctor if

an allergic reaction to this product occurs. Seek medical help right away.

If pregnant or breast-feeding,

ask a health professional before use

Keep out of reach of children.

In case of overdose, get medical help or contact a Poison Control Center right away.

Directions

adults and children take one 60 mg tablet with water every 12 hours; do not take more than 2 tablets in 24 hours

12 years of age and over

children under 12 years of age do not use

adults 65 years of age and older ask a doctor

consumers with kidney disease ask a doctor

Other information

■ safety sealed: do not use if carton is opened or if individual blister units are torn or opened ■ store between
20° and 25°C (68° and 77°F) ■ protect from excessive moisture

Inactive ingredients

colloidal silicon dioxide, croscarmellose sodium, hypromellose, iron oxide black, iron oxide red, iron oxide yellow,
lactose monohydrate, macrogol, magnesium stearate, microcrystalline cellulose, pregelatinized starch, titanium dioxide

Questions or comments?

contact 1-877-770-3183 Mon-Fri 8:00 AM EST to 5:00 PM PST